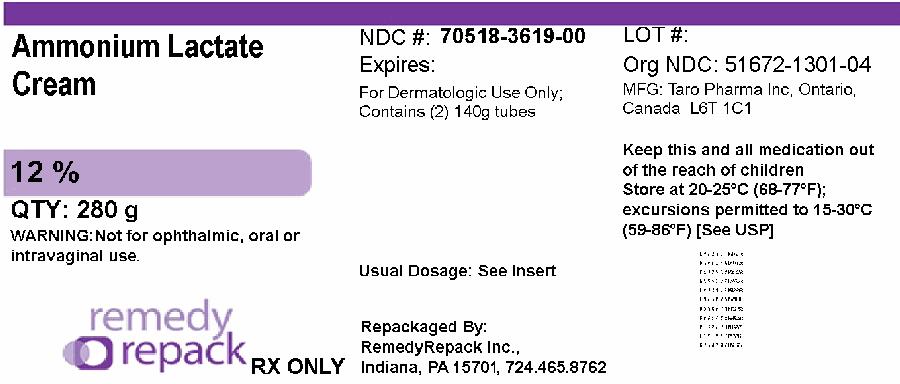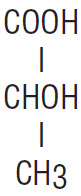 DRUG LABEL: Ammonium Lactate
NDC: 70518-3619 | Form: CREAM
Manufacturer: REMEDYREPACK INC.
Category: prescription | Type: HUMAN PRESCRIPTION DRUG LABEL
Date: 20250725

ACTIVE INGREDIENTS: AMMONIUM LACTATE 120 mg/1 g
INACTIVE INGREDIENTS: CETYL ALCOHOL; GLYCERIN; GLYCERYL MONOSTEARATE; LAURETH-4; LIGHT MINERAL OIL; MAGNESIUM ALUMINUM SILICATE; METHYLPARABEN; PROPYLPARABEN; PEG-100 STEARATE; POLYOXYL 40 STEARATE; PROPYLENE GLYCOL; WATER

Ammonium Lactate Cream 12%*

Rx only.

For Dermatological Use only.
Not for Ophthalmic, Oral or Intravaginal Use.

DESCRIPTION

* Ammonium Lactate Cream, 12% specially formulates 12% lactic acid, as ammonium lactate to provide a cream pH of 4.5 to 5.5. Ammonium Lactate Cream, 12% also contains cetyl alcohol, glycerin, glyceryl monostearate, laureth-4, light mineral oil, magnesium aluminum silicate, methylcellulose, methylparaben, propylparaben, polyoxyethylene-100 stearate, polyoxyl 40 stearate, propylene glycol, purified water and for pH adjustment: lactic acid. Lactic acid is a racemic mixture of 2-hydroxypropanoic acid and has the following structural formula:

CLINICAL PHARMACOLOGY

Lactic acid is an alpha-hydroxy acid. It is a normal constituent of tissues and blood. The alpha-hydroxy acids (and their salts) are felt to act as humectants when applied to the skin. This property may influence hydration of the stratum corneum. In addition, lactic acid, when applied to the skin, may act to decrease corneocyte cohesion. The mechanism(s) by which this is accomplished is not yet known.

An in vitrostudy of percutaneous absorption of ammonium lactate cream using human cadaver skin indicates that approximately 6.1% of the material was absorbed after 68 hours.

INDICATIONS AND USAGE

Ammonium Lactate Cream, 12% is indicated for the treatment of ichthyosis vulgaris and xerosis.

CONTRAINDICATIONS

Ammonium Lactate Cream, 12% is contraindicated in those patients with a history of hypersensitivity to any of the label ingredients.

WARNING

Sun exposure to areas of the skin treated with Ammonium Lactate Cream, 12% should be minimized or avoided (see PRECAUTIONSsection). The use of Ammonium Lactate Cream, 12% should be discontinued if any hypersensitivity is observed.

PRECAUTIONS

General

For external use only. Stinging or burning may occur when applied to skin with fissures, erosions, or that is otherwise abraded (for example, after shaving the legs). Caution is advised when used on the face because of the potential for irritation. The potential for post-inflammatory hypo- or hyperpigmentation has not been studied.

Information for Patients

Patients using Ammonium Lactate Cream, 12% should receive the following information and instructions:

1. This medication is to be used as directed by the physician, and should not be used for any disorder other than for which it was prescribed. It is for external use only. Avoid contact with the eyes, lips, or mucous membranes.
2. Patients should minimize or avoid use of this product on areas of the skin that may be exposed to natural or artificial sunlight, including the face. If sun exposure is unavoidable, clothing should be worn to protect the skin.
3. This medication may cause transient stinging or burning when applied to skin with fissures, erosions, or abrasions (for example, after shaving the legs).
4. If the skin condition worsens with treatment, the medication should be promptly discontinued.

Repackaged By / Distributed By: RemedyRepack Inc.

625 Kolter Drive, Indiana, PA 15701

(724) 465-8762

Carcinogenesis, Mutagenesis, Impairment of Fertility

The topical treatment of CD-1 mice with 12%, 21% or 30% ammonium lactate formulations for two years did not produce a significant increase in dermal or systemic tumors in the absence of increased exposure to ultraviolet radiation. The maximum systemic exposure of the mice in this study was 0.7 times the maximum possible systemic exposure in humans. However, a long-term photocarcinogenicity study in hairless albino mice suggested that topically applied 12% ammonium lactate cream enhanced the rate of ultraviolet light-induced skin tumor formation.

The mutagenic potential of ammonium lactate cream was evaluated in the Ames assay and in the mouse in vivomicronucleus assay, both of which were negative.

In dermal Segment I and III studies with ammonium lactate cream there were no effects observed in fertility or pre- or post-natal development parameters in rats at dose levels of 300 mg/kg/day (1800 mg/m^2/day), approximately 0.4 times the human topical dose.

Pregnancy

Teratogenic effects

Animal reproduction studies have been performed in rats and rabbits at doses up to 0.7 and 1.5 times the human dose, respectively (600 mg/kg/day, corresponding to 3600 mg/m^2/day in the rat and 7200 mg/m^2/day in the rabbit) and have revealed no evidence of impaired fertility or harm to the fetus due to ammonium lactate cream. There are, however, no adequate and well-controlled studies in pregnant women. Because animal reproduction studies are not always predictive of human response, Ammonium Lactate Cream, 12% should be used during pregnancy only if clearly needed.

Nursing Mothers

Although lactic acid is a normal constituent of blood and tissues, it is not known to what extent this drug affects normal lactic acid levels in human milk. Because many drugs are excreted in human milk, caution should be exercised when Ammonium Lactate Cream, 12% is administered to a nursing woman.

Pediatric Use

The safety and effectiveness of Ammonium Lactate Cream, 12% have been established in pediatric patients as young as 2 years old.

Geriatric Use

Clinical studies of Ammonium Lactate Cream, 12% did not include sufficient numbers of subjects aged 65 and over to determine whether they respond differently from younger subjects. Other reported clinical experience has not identified differences in responses between elderly and younger patients. In general, dose selection for an elderly patient should be cautious.

ADVERSE REACTIONS

In controlled clinical trials of patients with ichthyosis vulgaris, the most frequent adverse reactions in patients treated with Ammonium Lactate Cream, 12% were rash (including erythema and irritation) and burning/stinging. Each was reported in approximately 10 to 15% of patients. In addition, itching was reported in approximately 5% of patients.

In controlled clinical trials of patients with xerosis, the most frequent adverse reactions in patients treated with Ammonium Lactate Cream, 12% were transient burning, in about 3% of patients, stinging, dry skin and rash, each reported in approximately 2% of patients.

DOSAGE AND ADMINISTRATION

Apply to the affected areas and rub in thoroughly. Use twice daily or as directed by a physician.

HOW SUPPLIED

Ammonium Lactate Cream, 12% is available as follows:

NDC: 70518-3619-00

PACKAGING: 2 in 1 CARTON, 140 g in 1 TUBE TYPE 0

Store at 20° to 25°C (68° to 77°F)[see USP Controlled Room Temperature].

Repackaged and Distributed By:

Remedy Repack, Inc.

625 Kolter Dr. Suite #4 Indiana, PA 1-724-465-8762

Repackaged and Distributed By:

Remedy Repack, Inc.

625 Kolter Dr. Suite #4 Indiana, PA 1-724-465-8762

PACKAGE LABEL

DRUG: Ammonium Lactate

GENERIC: Ammonium Lactate

DOSAGE: CREAM

ADMINSTRATION: TOPICAL

NDC: 70518-3619-0

COLOR: white

PACKAGING: 140 g in 1 TUBE

OUTER PACKAGING: 2 in 1 CARTON

ACTIVE INGREDIENT(S):

- AMMONIUM LACTATE 120mg in 1g

INACTIVE INGREDIENT(S):

- CETYL ALCOHOL
- GLYCERIN
- GLYCERYL MONOSTEARATE
- LAURETH-4
- LIGHT MINERAL OIL
- MAGNESIUM ALUMINUM SILICATE
- METHYLPARABEN
- PROPYLPARABEN
- PEG-100 STEARATE
- POLYOXYL 40 STEARATE
- PROPYLENE GLYCOL
- WATER